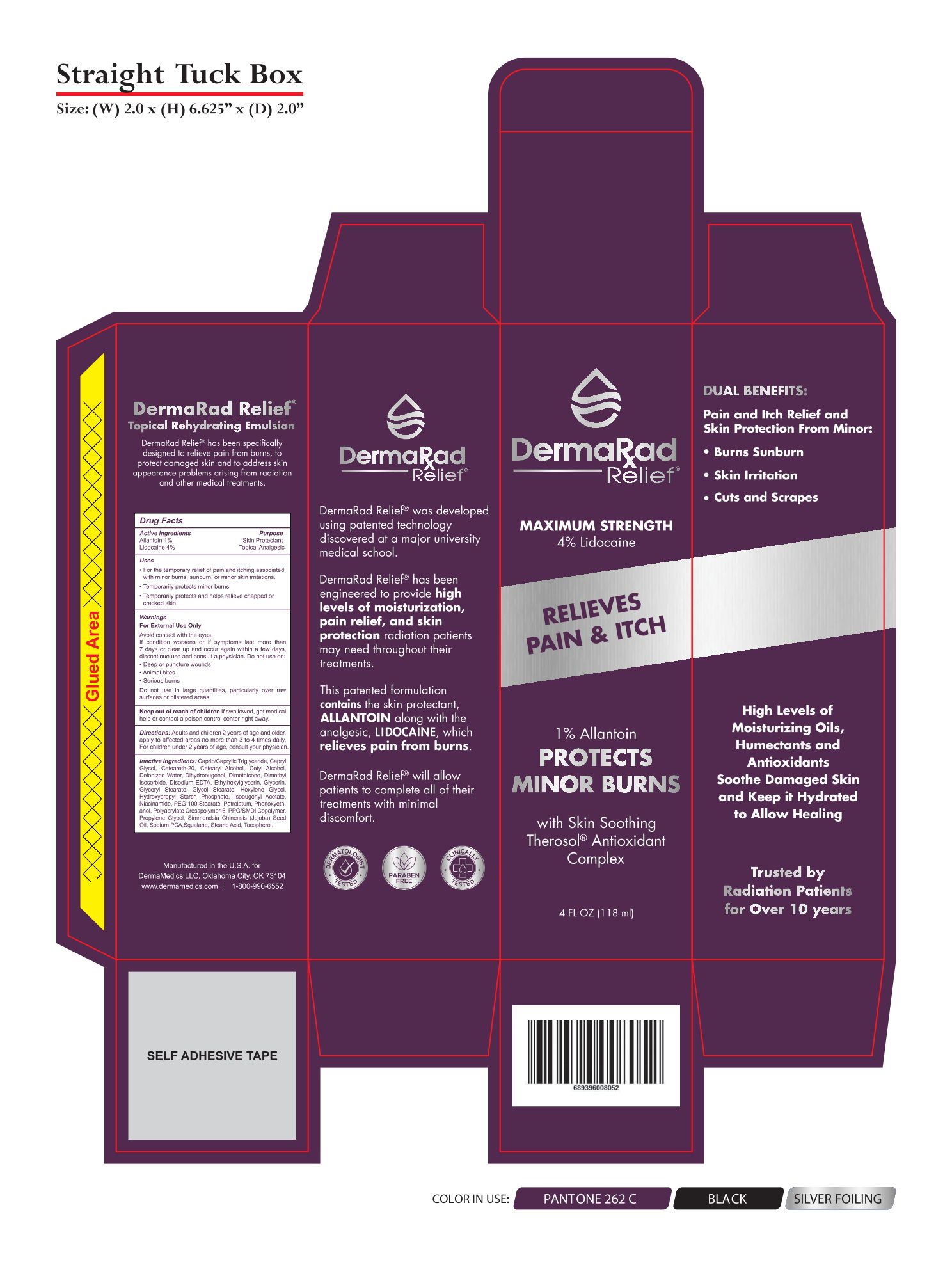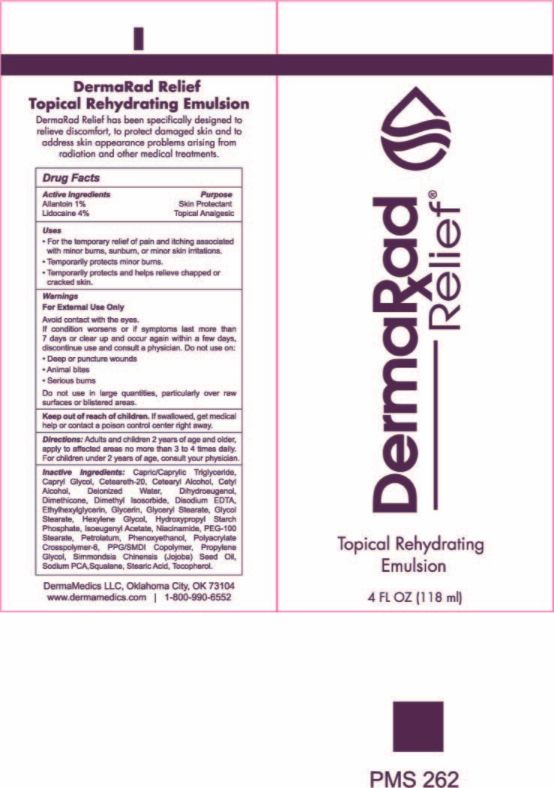 DRUG LABEL: DermaRad Relief
NDC: 76348-720 | Form: EMULSION
Manufacturer: RENU LABORATORIES, LLC
Category: otc | Type: HUMAN OTC DRUG LABEL
Date: 20250506

ACTIVE INGREDIENTS: ALLANTOIN 1.18 g/118 mL; LIDOCAINE 4.72 g/118 mL
INACTIVE INGREDIENTS: ALPHA-TOCOPHEROL; DIHYDROEUGENOL; PHENOXYETHANOL; CAPRYLYL GLYCOL; ETHYLHEXYLGLYCERIN; CETYL ALCOHOL; PPG-51/SMDI COPOLYMER; HEXYLENE GLYCOL; NIACINAMIDE; PROPYLENE GLYCOL; STEARIC ACID; JOJOBA OIL; WHITE PETROLATUM; CETOSTEARYL ALCOHOL; DIMETHICONE; POLYOXYL 20 CETOSTEARYL ETHER; DIMETHYL ISOSORBIDE; AMMONIUM ACRYLOYLDIMETHYLTAURATE, DIMETHYLACRYLAMIDE, LAURYL METHACRYLATE AND LAURETH-4 METHACRYLATE COPOLYMER, TRIMETHYLOLPROPANE TRIACRYLATE CROSSLINKED (45000 MPA.S); GLYCERYL STEARATE/PEG-100 STEARATE; GLYCOL STEARATE; ISOEUGENYL ACETATE; PEG-100 STEARATE; WATER; MEDIUM-CHAIN TRIGLYCERIDES; SODIUM PYRROLIDONE CARBOXYLATE; GLYCERIN; EDETIC ACID; SODIUM HYDROXIDE; SQUALANE; HYDROXYPROPYL CORN STARCH (5% SUBSTITUTION BY WEIGHT)

DermaRad Relief Topical Rehydrating Emulsion

Active Ingredients

Allantoin 1%

Lidocaine 4%

Warnings

For External Use Only

Avoid contact with the eyes.

If condition worsens or if symptoms last more than

7 days or clear up and occur again within a few days,

discontinue use and consult a physician. Do not use on:

- Deep or puncture wounds
- Animal bites
- Serious burns

Do not use in large quantities, particularly over raw surfaces or blistered areas.

Do not use on:

- Deep or puncture wounds
- Animal bites
- Serious burns

Do not use in large quantities, particularly over raw surfaces or blistered areas.

Purpose

Skin Protectant

Topical Analgesic

QUESTIONS

DermaMedics LLC, Oklahoma City, OK 73104

www.dermamedics.com

1-800-990-6552

DOSAGE AND ADMINISTRATION

Directions: Adults and children 2 years of age and older,

apply to affected areas no more than 3 to 4 times daily.

For children under 2 years of age, consult your physician.

Uses

- For the temporary relief of pain and itching associated with minor burns, sunburn, or minor skin irritations.
- Temporarily protects minor burns.
- Temporarily protects and helps relieve chapped or cracked skin.

Inactive Ingredients:

Capric/Caprylic Triglyceride, Capryl Glycol, Ceteareth-20, Cetearyl Alcohol, Cetyl Alcohol, Deionized Water, Dihydroeugenol,

Dimethicone, Dimethyl Isosorbide, Disodium EDTA, Ethylhexylglycerin, Glycerin, Glyceryl Stearate, Glycol Stearate, Hexylene Glycol, Hydroxypropyl Starch Phosphate, Isoeugenyl Acetate, Niacinamide, PEG-100 Stearate, Petrolatum, Phenoxyethanol, Polyacrylate

Crosspolymer-6, PPG/SMDI Copolymer, Propylene Glycol, Simmondsia Chinensis (Jojoba) Seed Oil, Sodium PCA, Squalane, Stearic Acid, Tocopherol.

STATEMENT OF IDENTITY

DermaRad Relief

Topical Rehydrating Emulsion

Keep out of reach of children

DermaRad Relief Product Label

DERMARAD LABEL AND OUTER BOX